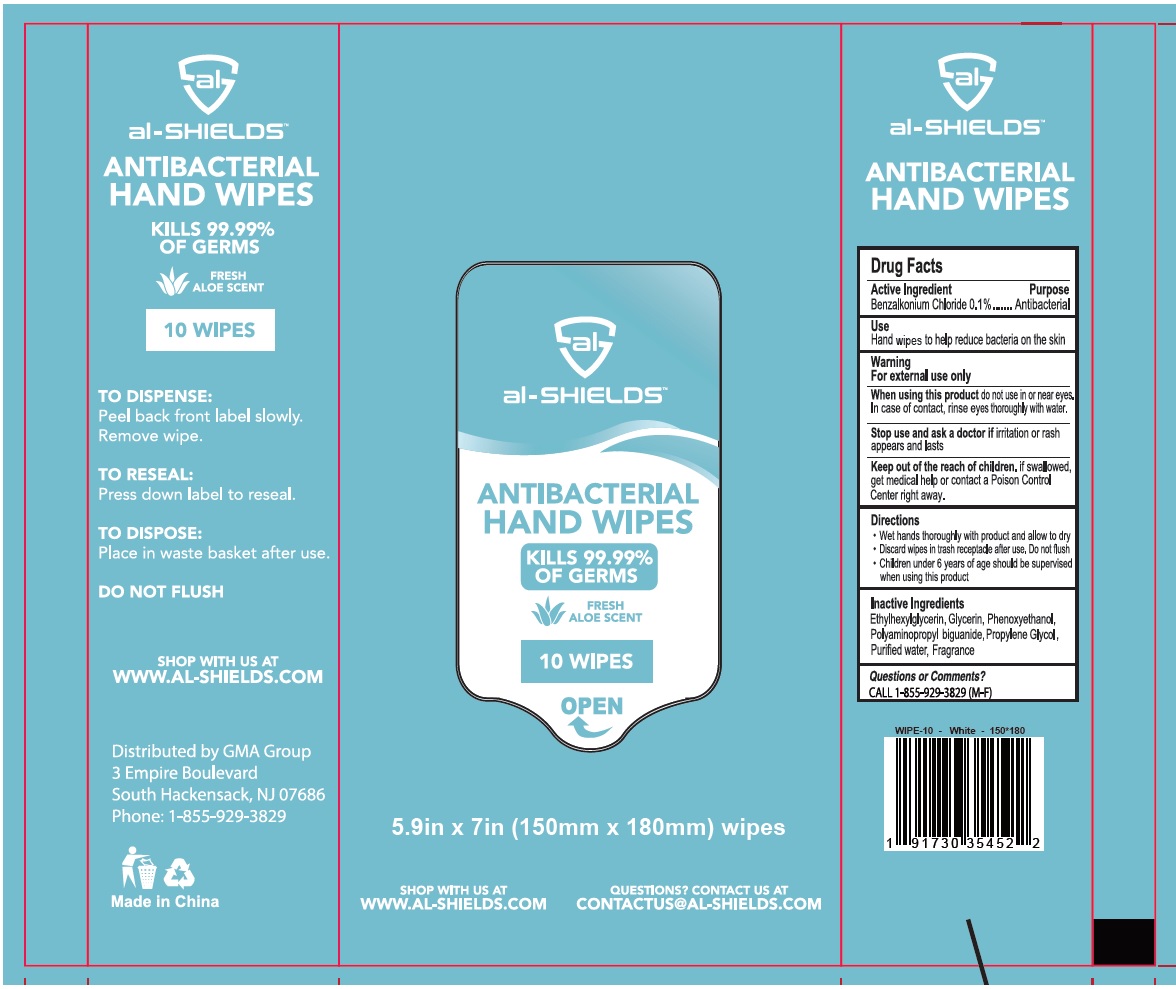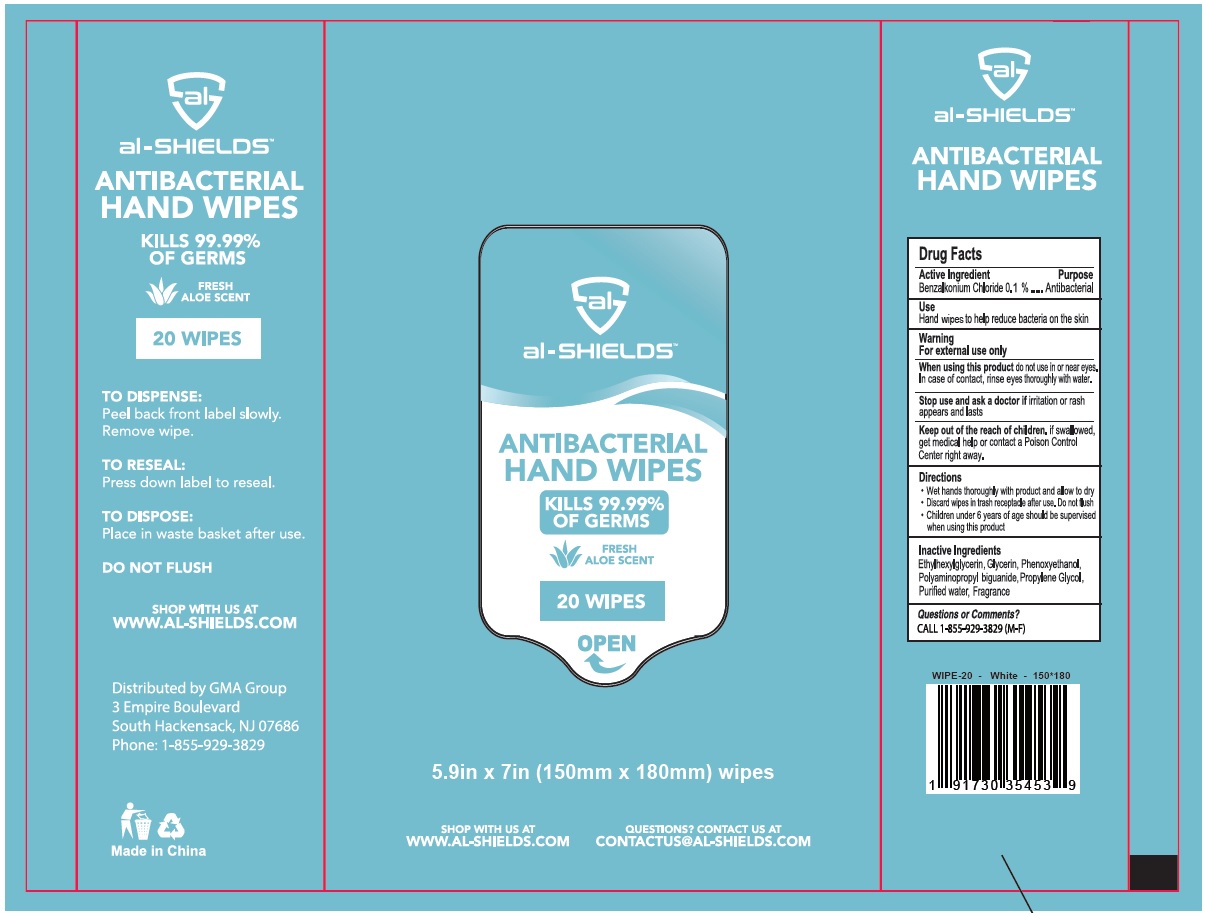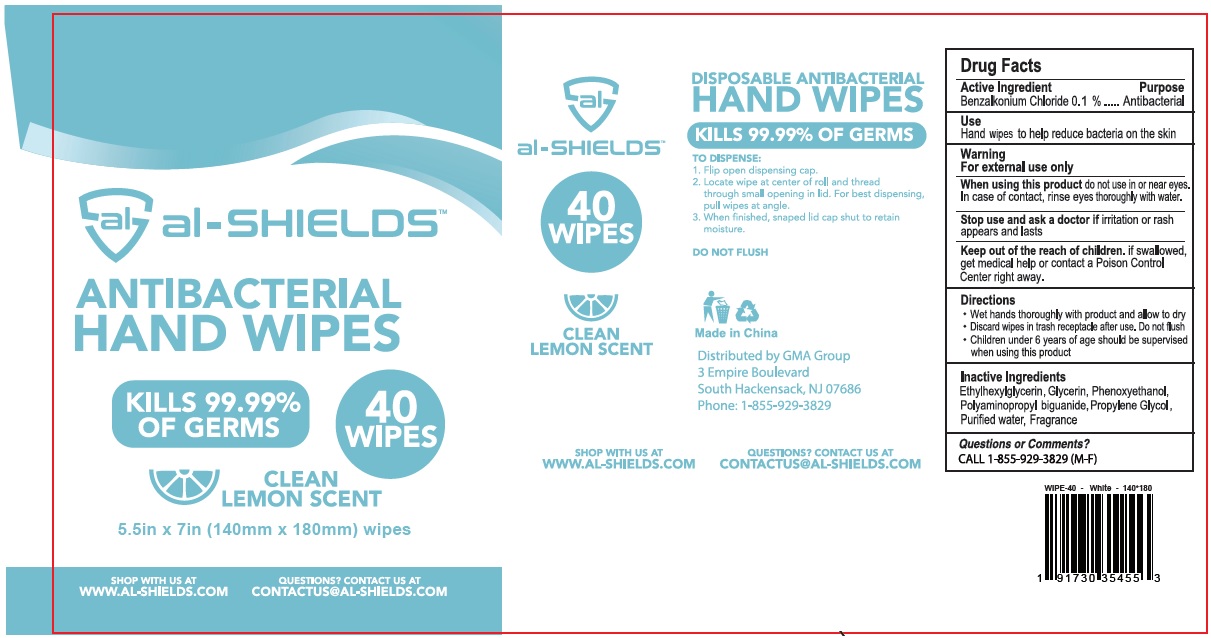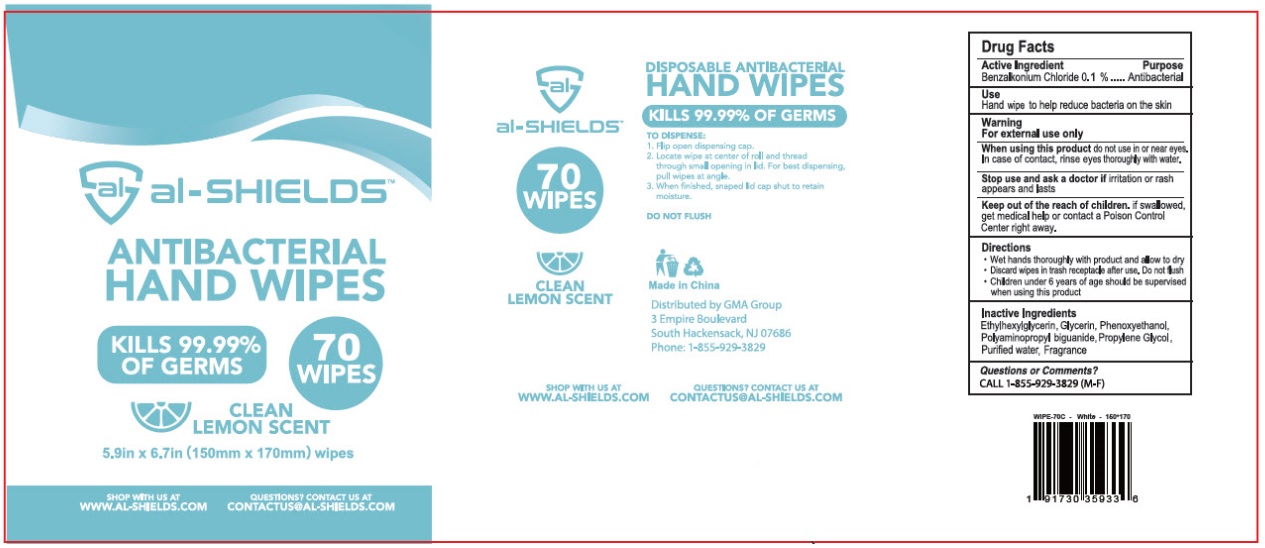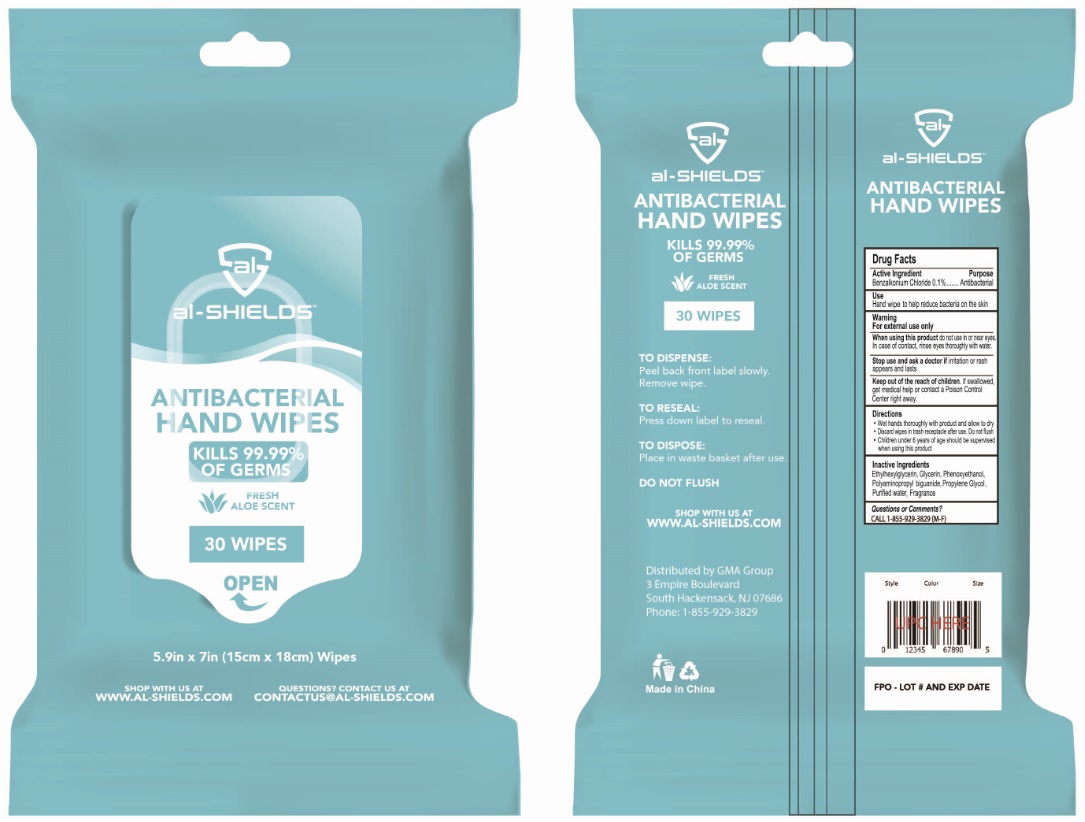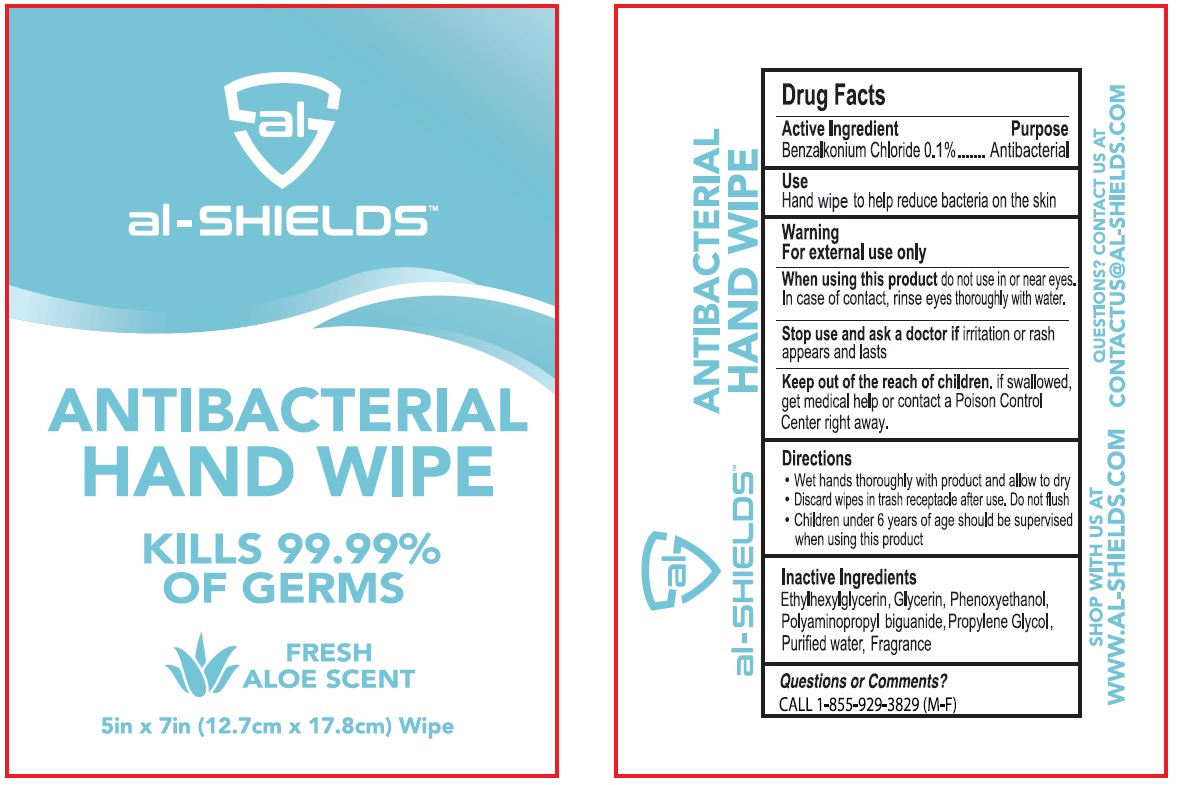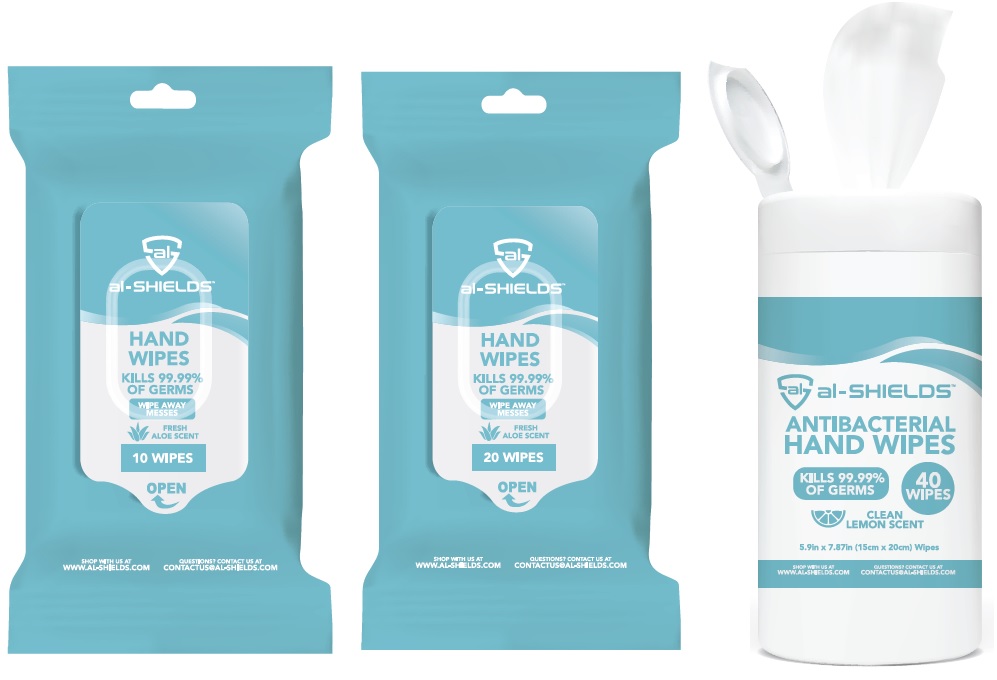 DRUG LABEL: al-SHIELDS ANTIBACTERIAL HAND WIPES
NDC: 79848-100 | Form: CLOTH
Manufacturer: Gma Accessories Inc.
Category: otc | Type: HUMAN OTC DRUG LABEL
Date: 20200807

ACTIVE INGREDIENTS: BENZALKONIUM CHLORIDE 0.1 g/100 mL
INACTIVE INGREDIENTS: ETHYLHEXYLGLYCERIN; GLYCERIN; PHENOXYETHANOL; POLYAMINOPROPYL BIGUANIDE; PROPYLENE GLYCOL; WATER

al-SHIELDS™ ANTIBACTERIAL HAND WIPES

Active Ingredient

Benzalkonium Chloride 0.1%

Purpose

Antibacterial

Use

Hand wipes to help reduce bacteria on the skin

Warnings

For external use only

When using this product do not use in or near the eyes. In case of contact, rinse eyes thoroughly with water.

Stop use and ask a doctor if irritation or rash appears and lasts

KEEP OUT OF REACH OF CHILDREN

Keep out of the reach of children. if swallowed, get medical help or contact a Poison Control Center right away.

Directions

- Wet hands thoroughly with product and allow to dry
- Discard wipes in trash receptacle after use. Do not flush
- Children under 6 years of age should be supervised when using this product

Inactive ingredients

Ethylhexylglycerin, Glycerin, Phenoxyethanol, Polyaminopropyl biguanide, Propylene Glycol, Purified water, Fragrance

Questions or Comments?

CALL 1-855-929-3829 (M-F)

KILLS 99.99% OF GERMS

FRESH ALOE SCENT

TO DISPENSE:

Peel back front label slowly.

Remove wipe.

TO RESEAL:

Press down label to reseal.

TO DISPOSE:

Place in water basket after use.

DO NOT FLUSH

SHOP WITH US AT

WWW.AL-SHIELDS.COM

QUESTIONS? CONTANT US AT

CONTACTUS@AL-SHIELDS.COM

Distributed by GMA Group

3 Empire Boulevard

South Hackensack, NJ 07686

Phone: 1-855-929-3829

Made in China

SHOP WITH US AT

WWW.AL-SHIELDS.COM

QUESTIONS? CONTACT US AT

CONTACTUS@AL-SHIELDS.COM